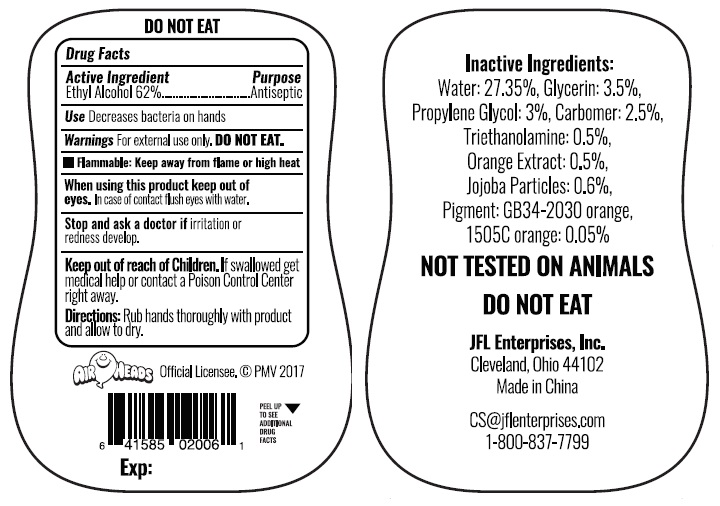 DRUG LABEL: Hand Sanitizer Orange
NDC: 71246-4005 | Form: GEL
Manufacturer: JFL ENTERPRISES, INC
Category: otc | Type: HUMAN OTC DRUG LABEL
Date: 20180101

ACTIVE INGREDIENTS: ALCOHOL 62 mL/100 mL
INACTIVE INGREDIENTS: PROPYLENE GLYCOL; WATER; GLYCERIN; CARBOMER HOMOPOLYMER TYPE B (ALLYL SUCROSE CROSSLINKED); TRIETHANOLAMINE 2-CYCLOHEXYL-4,6-DINITROPHENOLATE; PIGMENT ORANGE 34; PIGMENT BLUE 16; JOJOBA ACID; ORANGE

ANTIBACTERIAL HAND GEL Air Heads Orange

Active ingredient

Alcohol 62%

Purpose

Antiseptic Hand Sanitizer

Use

Decrease bacteria on hands

Warnings

External Use Only. DO NOT EAT.

Keep out of reach of children

if swallowed
get medical help or contact a Poison Control Center right away.

Directions

Rub hands thoroughly with product and allow to dry.

Inactive Ingredient

Carbomer, Glycerin, Jojoba Particles, Pigment Orange GB34-2030, Orange 1505C, Propylene Glycol, Triethanolamine, Water.

Stop and Ask a doctor if

Irritation or redness develop.